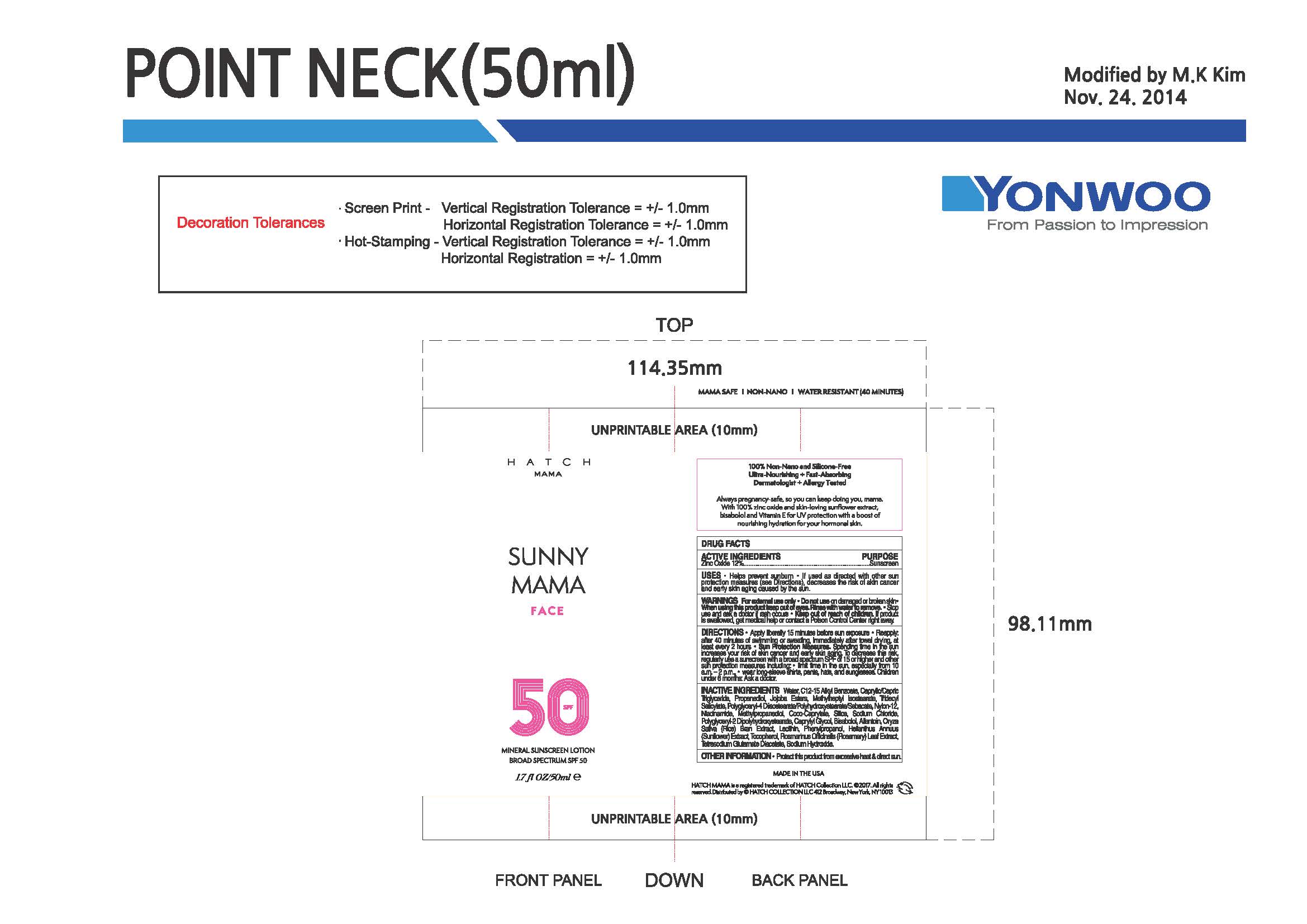 DRUG LABEL: HATCH MAMA SUNNY MAMA Face Mineral Sunscreen Broad Spectrum SPF 50
NDC: 82117-200 | Form: LOTION
Manufacturer: Hatch Collection LLC
Category: otc | Type: HUMAN OTC DRUG LABEL
Date: 20220222

ACTIVE INGREDIENTS: ZINC OXIDE 12 g/100 g
INACTIVE INGREDIENTS: WATER; C12-15 ALCOHOLS; CAPRYLIC/CAPRIC ACID; PROPANEDIOL; JOJOBA ACID; METHYLHEPTYL ISOSTEARATE; POLYGLYCERYL-4 DIISOSTEARATE/POLYHYDROXYSTEARATE/SEBACATE; NYLON-12; NIACINAMIDE; METHYLPROPANEDIOL; COCO-CAPRYLATE; SILICON DIOXIDE; POLYGLYCERYL-2 DIPOLYHYDROXYSTEARATE; SODIUM CHLORIDE; ORYZA SATIVA WHOLE; HELIANTHUS ANNUUS WHOLE; BISABOLOL OXIDE A; ALLANTOIN; LECITHIN, SOYBEAN; CAPRYLYL GLYCOL; GLYCERIN; TOCOPHEROL; CAMELLIA SINENSIS SEED; ROSMARINUS OFFICINALIS FLOWER; TETRASODIUM GLUTAMATE DIACETATE; SODIUM HYDROXIDE

DRUG FACTS

Active Ingredients

Zinc Oxide 12%

Uses

• helps prevent sunburn • if used as directed with other
sun protection measures (see Directions), decreases the
risk of skin cancer and early skin aging caused by the sun

Warnings

For external use only
Do not use on damaged or broken skin
When using this product keep out of eyes. Rinse with water to remove.
Stop use and ask a docor if rash occurs
Keep out of reach of children. If swalled, get medical help or contact a Poison Control Center right away.

Directions

• apply liberally 15 minutes before sun exposure
• reapply:
• after 40 minutes of swimming or sweating
• immediately after towel drying
• at least every 2 hours
• Sun Protection Measures. Spending time in the sun increases your risk
of skin cancer and early skin aging. To decrease this risk, regularly use
a sunscreen with a broad spectrum SPF of 15 or higher and other sun
protection measures including:
• limit time in the sun, especially from 10 a.m. – 2 p.m.
• wear long-sleeve shirts, pants, hats, and sunglasses
• children under 6 months: Ask a doctor

Inactive ingredients

Water, C12-15 Alkyl Benzoate, Caprylic/Capric Triglyceride, Propanediol, Jojoba Esters, Methylheptyl Isostearate, Tridecyl Salicylate, Polyglyceryl-4 Diisostearate/Polyhydroxystearate/Sebacate, Nylon-12, Niacinamide, Methylpropanediol, Coco-Caprylate, Silica, Sodium Chloride, Polyglyceryl-2 Dipolyhydroxystearate, Caprylyl Glycol, Bisabolol, Allantoin, Oryza Sativa (Rice) Bran Extract, Lecithin, Phenylpropanol, Helianthus Annuus (Sunflower) Extract, Tocopherol, Rosmarinus Officinalis (Rosemary) Leaf Extract, Tetrasodium Glutamate Diacetate, Sodium Hydroxide

Other Information

• protect the product in this container from excessive
heat and direct sun